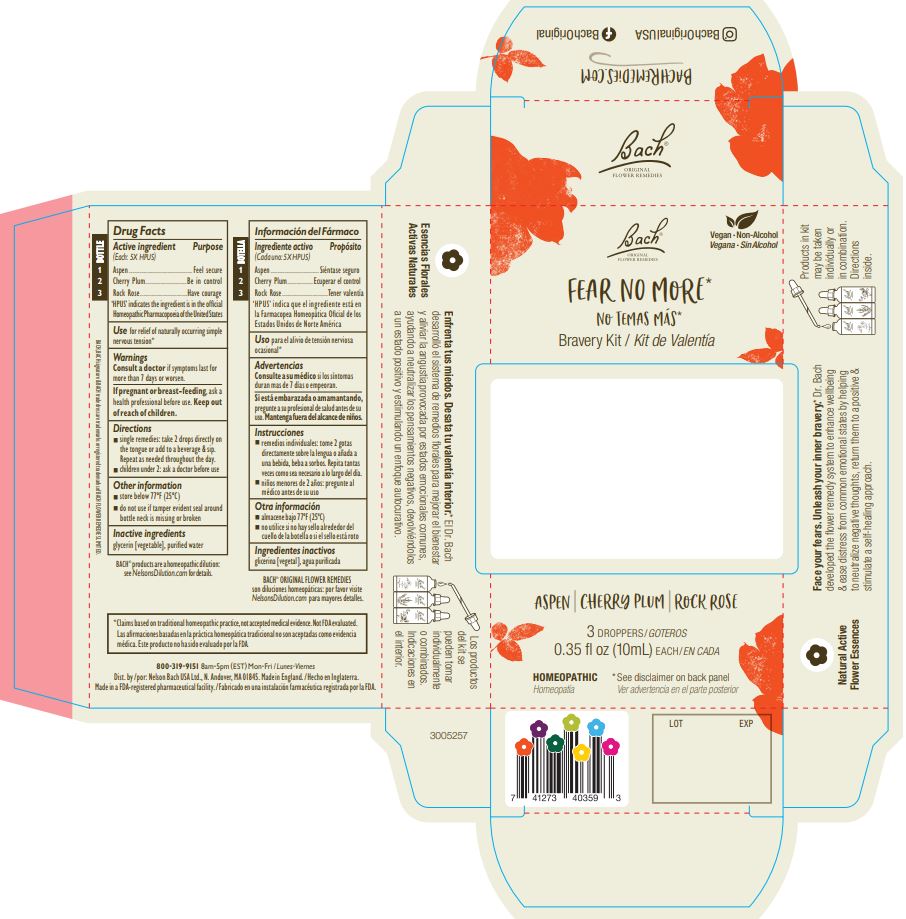 DRUG LABEL: Bach Fear No More Bravery Kit
NDC: 57687-313 | Form: KIT | Route: ORAL
Manufacturer: Nelson Bach USA Limited
Category: homeopathic | Type: HUMAN OTC DRUG LABEL
Date: 20231017

ACTIVE INGREDIENTS: HELIANTHEMUM NUMMULARIUM FLOWER 5 [hp_X]/0.095 mL; POPULUS TREMULA FLOWERING TOP 5 [hp_X]/0.095 mL; PRUNUS CERASIFERA FLOWER 5 [hp_X]/0.095 mL
INACTIVE INGREDIENTS: WATER; GLYCERIN; GLYCERIN; WATER; GLYCERIN; WATER

Bach Fear No More Bravery Kit

ACTIVE INGREDIENT

Active ingredient (Each 5X HPUS)............... Purpose

Bottle 1: Aspen...............................................Feel secure

Bottle 2: Cherry Plum.....................................Be in control

Bottle 3: Rock Rose.......................................Have courage

'HPUS' indicates ingredients are in the official Homeopathic Pharmacopoeia of the United States

Use

For relief of naturally occuring simple nervous tension

Warnings

Consult a doctor if symptoms last for more than 7 days or worsen.

PREGNANCY OR BREAST FEEDING

If pregnant or breast-feeding, ask a health professional before use.

Keep out of reach of children.

Directions

■ single remedies: take 2 drops directly on the tongue or add to a beverage & sip. Repeat as needed throughout the day.
■ children under 2: ask a doctor before use

Other information

■ store below 77ºF (25ºC)
■ do not use if tamper evident seal around bottle neck is missing or broken

Inactive ingredients

glycerin [vegetable], purified water